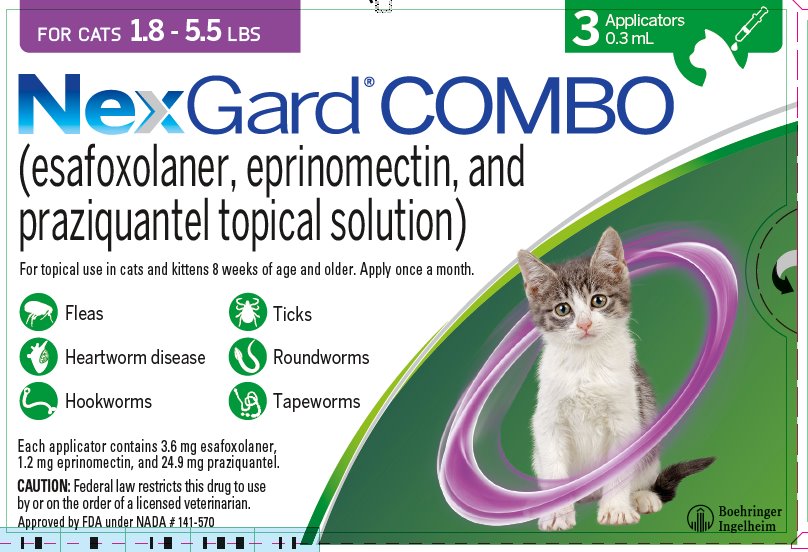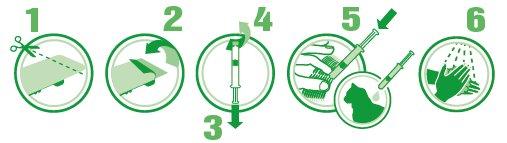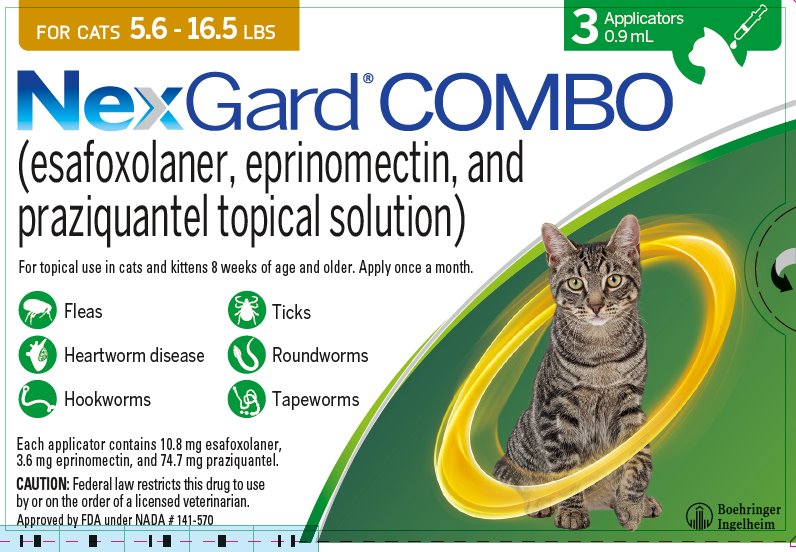 DRUG LABEL: NexGard COMBO
NDC: 0010-4120 | Form: SOLUTION
Manufacturer: Boehringer Ingelheim Animal Health USA Inc.
Category: animal | Type: PRESCRIPTION ANIMAL DRUG LABEL
Date: 20240927

ACTIVE INGREDIENTS: ESAFOXOLANER 12 mg/1 mL; EPRINOMECTIN 4 mg/1 mL; PRAZIQUANTEL 83 mg/1 mL

NexGard® COMBO
(esafoxalaner, eprinomectin, and praziquantel topical solution)

For topical use in cats only

Caution:

Federal law restricts this drug to use by or on the order of a licensed veterinarian.

Description:

NexGard® COMBO is a topical solution containing esafoxolaner, eprinomectin and praziquantel available in 0.3 mL and 0.9 mL unit applicators to treat cats from 1.8 lbs to 33 lbs. Each mL of NexGard® COMBO contains 12 mg of esafoxolaner, 4 mg of eprinomectin, and 83 mg of praziquantel. Inactive ingredients: dimethyl isosorbide, unstabilized glycerol formal, and butylated hydroxytoluene.

Esafoxolaner is a member of the aryl isoxazoline class of compounds. Its chemical name is 4-[(5S)-5-[3-chloro-5-(trifluoromethyl)phenyl]-5-(trifluoromethyl)-4, 5-dihydro-1,2-oxazol-3-yl]-N-{2-oxo-2-[(2,2,2-trifluoroethyl)amino]ethyl}-1-naphthamide.

Eprinomectin belongs to the avermectin class of anthelmintics and is a mixture of homologous components referred to as eprinomectin B1a and B1b. The chemical name for eprinomectin B1a is (4”R)-acetylamino-5-O-demethyl-4”-deoxyavermectin A1a. The chemical name for eprinomectin B1b is (4”R)-acetylamino-5-O-demethyl-25-de(1-methylpropyl)- 4”-deoxy-25-(1-methylethyl)avermectin A1a.

Praziquantel is a pyrazinoisoquinoline anthelmintic. Its chemical name is 2-(Cyclohexylcarbonyl)- 1,2,3,6, 7,11b-hexahydro-4H-pyrazino[2,1-a]-isoquinolin-4-one.

Indications:

NexGard® COMBO is indicated for the prevention of heartworm disease caused by Dirofilaria immitis and for the treatment and control of roundworm (fourth stage larval and adult Toxocara cati), hookworm (fourth stage larval and adult Ancylostoma tubaeforme; adult Ancylostomabraziliense), and tapeworm (Dipylidium caninum) infections. NexGard® COMBO kills adult fleas (Ctenocephalides felis) and is indicated for the treatment and prevention of flea infestations and the treatment and control of Ixodes scapularis (black-legged tick) and Amblyomma americanum (lone star tick) infestations for one month in cats and kittens 8 weeks of age and older, and weighing 1.8 lbs or greater.

Dosage and Administration:

NexGard® COMBO is dosed at a minimum of 0.055 mL/lb (0.12 mL/kg), which delivers a minimum dose of 0.65 mg/lb (1.44 mg/kg) esafoxolaner, 0.22 mg/lb (0.48 mg/kg) eprinomectin, and 4.53 mg/lb (9.98 mg/kg) praziquantel.

For heartworm disease prevention, apply once monthly for at least three months after last exposure to mosquitoes (see Effectiveness).

Administer the entire contents of a NexGard® COMBO unit applicator topically once a month as specified in the following table:

Dosing Schedule

Cat Weight (lb) | Volume (mL) | Esafoxolaner (mg) | Eprinomectin (mg) | Praziquantel (mg)
1.8- 5.5 | 0.3 | 3.6 | 1.2 | 24.9
5.6-16.5 | 0.9 | 10.8 | 3.6 | 74.7
16.6-22 | 0.3 + 0.9 | 14.4 | 4.8 | 99.6
22.1-33 | 0.9 + 0.9 | 21.6 | 7.2 | 149.4

A veterinarian or veterinary technician should demonstrate or instruct the pet owner regarding the appropriate technique for applying NexGard® COMBO topically to cats and kittens prior to first use.

Keep product in original packaging until ready to use.

1. Use scissors to cut the blister along the dotted line.
2. Then pull the lid away.
3. Remove the applicator from the package and hold it upright. Pull back the plunger slightly.
4. Twist and pull off the cap.
5. Part the hair on the midline of the neck, between the base of the skull and the shoulder blades until the skin is visible. Place the tip of the applicator on the skin and apply the entire contents directly onto the skin in one spot. The product should be applied to dry skin on an area where the cat cannot lick it off. If the weight of the cat requires a second application, apply the contents in the same manner as described above in the same location.
6. Wash hands after use with soap and water.

Heartworm Prevention:

For the prevention of heartworm disease, NexGard® COMBO should be administered once a month year-round. At a minimum, administration of NexGard® COMBO should start at least 1 month before the cat’s first expected exposure to mosquitoes and monthly thereafter until at least 3 months after the cat’s last seasonal exposure to mosquitoes (see Effectiveness). If a dose is missed and a 30-day interval between doses is exceeded, administer NexGard® COMBO immediately and resume the monthly dosing schedule. Treatment with fewer than 3 monthly doses may not provide complete heartworm prevention. When replacing another monthly heartworm preventive product in a heartworm prevention program, the first treatment with NexGard® COMBO should be given within one month of the last dose of the former medication. At the discretion of the veterinarian, cats older than 6 months of age may be tested to determine the presence of existing heartworm infection before treatment with NexGard® COMBO. Cats already infected with adult heartworms can be given NexGard® COMBO monthly to prevent further infections.

Flea Treatment and Prevention:

For the treatment and prevention of flea infestations, the use of NexGard® COMBO may begin at any time of year. NexGard® COMBO should be administered year-round at monthly intervals or begin at least one month before fleas become active. However, an environmental infestation may persist for a short time after beginning treatment with NexGard® COMBO because of the development of adult fleas from eggs that were laid prior to the initiation of treatment.

Tick Treatment and Control:

For the treatment and control of infestations with Ixodes scapularis and Amblyomma americanum, the use of NexGard® COMBO may begin at any time of year. NexGard® COMBO should be administered year-round at monthly intervals or begin at least one month before the ticks become active.

Treatment and Control of Roundworms, Hookworms, and Tapeworms:

NexGard® COMBO provides treatment and control of roundworms (adult and fourth stage larval Toxocara cati), hookworms (adult and fourth stage larval Ancylostoma tubaeforme; adult Ancylostoma braziliense), and tapeworms (Dipylidium caninum). For the treatment of hookworm, roundworms and tapeworm infections, NexGard® COMBO should be administered once as a single dose. Monthly use of NexGard® COMBO will control any subsequent infections. Cats may be exposed to and can become infected with roundworms, hookworms, and tapeworms throughout the year, regardless of season or climate.

Contraindications:

There are no known contraindications for the use of NexGard® COMBO.

Human Warnings:

Not for human use. Keep this and all drugs out of sight and reach of children.

Avoid direct contact with application site for 4 hours or until visibly dry.

This product may act as a mild to moderate eye irritant.

Keep product in the original packaging until use. Wash hands after product administration. If the product accidentally gets into the eyes, rinse thoroughly with water. If wearing contact lenses, flush the eyes first with water and then remove the lenses and continue to flush thoroughly with water. In case of accidental ingestion, or if skin or eye irritation occurs, contact a poison control center or physician for treatment advice.

Precautions:

Esafoxolaner, one of the ingredients in NexGard® COMBO, is a member of the isoxazoline class. This class has been associated with neurologic adverse reactions including tremors, ataxia, and seizures. Seizures have been reported in cats receiving isoxazoline class drugs, even in cats without a history of seizures. Use with caution in cats with a history of seizures or neurologic disorders.

Do not administer orally. Cats may salivate excessively if NexGard® COMBO is accidentally administered orally or is ingested through licking/grooming the application site (see Target Animal Safety).

The safety of NexGard® COMBO has not been fully evaluated in breeding, pregnant, or lactating cats.

The safety of NexGard® COMBO has not been tested in kittens less than 8 weeks of age or weighing less than 1.8 lbs (0.8 kg).

Adverse Reactions:

In a field safety and effectiveness study, which included a total of 201 households and 380 treated cats (244 cats treated with NexGard® COMBO, 136 cats treated with an active control), the safety of NexGard® COMBO was evaluated over a 90-day period through in-clinic physical examinations or through reporting of abnormalities by the owner. The most frequently reported reactions in the NexGard® COMBO and active control groups are presented in the following table.

Adverse Reactions by Treatment Group

EVENT | Treatment Group
EVENT | NEXGARD® COMBO |  | Active Control
EVENT | n1 | % (n=244) | n2 | % (n=136)
Vomiting | 16 | 6.56 | 8 | 5.88
Application Site Hair Change | 9 | 3.69 | 0 | 0.00
Anorexia | 7 | 2.87 | 4 | 2.94
Lethargy | 6 | 2.46 | 5 | 3.68
Bacterial skin infection | 4 | 1.64 | 1 | 0.74
Itching | 4 | 1.64 | 0 | 0.00
Sneezing | 4 | 1.64 | 5 | 3.68
Skin Peeling | 3 | 1.23 | 2 | 1.47
Diarrhea | 3 | 1.23 | 3 | 2.21
Epiphora | 3 | 1.23 | 1 | 0.74
Hypersalivation | 3 | 1.23 | 0 | 0.00
Hyperthermia | 3 | 1.23 | 0 | 0.00
Alopecia | 2 | 0.82 | 0 | 0.00
Dermal thickening | 2 | 0.82 | 0 | 0.00
Ear Pruritus | 2 | 0.82 | 1 | 0.74
Application Site Redness | 2 | 0.82 | 0 | 0.00
Conjunctivitis | 1 | 0.41 | 1 | 0.74

^1Number of cats treated with NexGard® COMBO with the identified abnormality.

^2Number of cats treated with Active Control with the identified abnormality.

Contact Information:

To report suspected adverse events, for technical assistance or to obtain a copy of the SDS, contact Boehringer Ingelheim Animal Health USA Inc. at 1-888-637-4251 or www.nexgardforpets.com.

For additional information about reporting adverse drug experiences for animal drugs, contact FDA at 1-888-FDA-VETS or online at www.fda.gov/reportanimalae.

The Safety Data Sheet (SDS) provides additional occupational safety information. For customer service or to obtain product information, including the SDS, call 1-888-637-4251.

Clinical Pharmacology:

Mode of Action:

Esafoxolaner is a member of the isoxazoline family, shown to bind at a site to inhibit insect and acarine ligand-gated chloride channels, in particular those gated by the neurotransmitter gamma-aminobutyric acid (GABA), thereby blocking pre- and post-synaptic transfer of chloride ions across cell membranes. Prolonged esafoxolaner-induced hyperexcitation results in uncontrolled activity of the central nervous system and death of insects and acarines. The selective toxicity of esafoxolaner between insects/acarines and mammals may be inferred by the differential sensitivity of the insects/acarines’ GABA receptors versus mammalian GABA receptors.

Eprinomectin is an endectocide in the macrocyclic lactone class that binds to glutamate gated chloride channels that are present in invertebrate nerve and muscle cells and increases the permeability of the cell membrane to chloride ions that triggers hyperpolarization of the nerve or muscle cell in susceptible parasites, resulting in paralysis and death of the parasite.

Praziquantel’s mode of action is not precisely known, but treated tapeworms undergo muscular paralysis accompanied by a rapid influx of calcium ions and the disruption of the tegument.

Pharmacokinetics:

After a single topical administration to healthy male and female cats of a combined topical formulation containing esafoxolaner (12 mg/mL), eprinomectin (4 mg/mL), and praziquantel (83 mg/mL), at dose volumes of 0.06, 0.12, or 0.24 mL/kg, there was a dose proportional increase in the exposure of each ingredient based on maximum plasma concentration (Cmax) and area under the plasma concentration time curve (AUC). After repeated monthly doses of the combined topical formulation at the target dose of 1.44 mg/kg esafoxolaner, 0.48 mg/kg eprinomectin, and 9.98 mg/kg praziquantel, steady state was reached by the fourth dose for esafoxolaner and after the second dose for eprinomectin and praziquantel. Additionally, modest accumulation was observed for esafoxolaner (approximately 3-fold) and praziquantel (approximately 1.5- to 2-fold) between the first and fifth dose, whereas no accumulation was observed for eprinomectin.

Effectiveness:

Heartworm Prevention:

In well-controlled laboratory studies, NexGard® COMBO (esafoxolaner, eprinomectin, and praziquantel topical solution) was 100% effective in preventing the development of heartworms in cats inoculated with infective larvae of Dirofilaria immitis 30 days prior to the first of three consecutive monthly treatments.

Flea Treatment and Prevention:

In a well-controlled laboratory study, NexGard® COMBO killed >92% of fleas within 24 hours. During subsequent weekly infestations, NexGard® COMBO killed ≥95.5% of fleas within 24 hours through Day 31 and killed fleas before they could lay eggs. The effectiveness against adult fleas at 24 hours post-infestation in the treated cats virtually eliminated flea egg production (99.8 – 100% control of flea egg production by 24 hours) throughout the remainder of the month. In a field safety and effectiveness study in the United States, conducted in households with existing flea infestations, the effectiveness of NexGard® COMBO against fleas was 97.8%, 99.6%, and 99.9% when assessed on Days 30, 60, and 90, respectively. Cats with signs of flea allergy dermatitis showed improvement in alopecia, dermatitis/pyodermatitis, pruritus, erythema, papules, and scaling, as a direct result of eliminating fleas.

Tick Treatment and Control:

In well-controlled laboratory studies, NexGard® COMBO demonstrated ≥95.1% effectiveness against Ixodes scapularis 48 hours post-infestation for a month and ≥95.6% effectiveness against Amblyomma americanum 72 hours post-infestation for a month.

Treatment and Control of Roundworms, Hookworms, and Tapeworms:

In 2 well-controlled laboratory studies, NexGard® COMBO provided 98.9% and 100% effectiveness against natural and/or induced roundworm infections with the dose-limiting gastrointestinal nematode species (adult Toxocara cati), respectively.

Effectiveness studies against fourth stage larval Toxocara cati and hookworms (adult and fourth stage larval Ancylostoma tubaeforme; adult Ancylostoma braziliense) were conducted with an early formulation. The doses of eprinomectin in this early formulation are equivalent to that of the final formulation of NexGard® COMBO.

In well-controlled laboratory studies, NexGard® COMBO provided on average 92.8% effectiveness against natural and/or induced infections with Dipylidium caninum.

Target Animal Safety:

Margin of Safety Study:

NexGard® COMBO was applied topically to healthy kittens (8 to 9 weeks of age) at 1X, 3X, or 5X the maximum exposure dose six times at 28-day intervals; kittens in the control group were dosed with mineral oil. One kitten in the 5X group exhibited recumbency, tremors, hypothermia, ataxia, disorientation, and pupil dilation (responsive to light) 9 hours after the third dose. This kitten received supportive care, including washing the application site, and recovered within 48 hours post-dose. During necropsy, a dark red subcutaneous area (≤5mm diameter) was observed in the treatment site area of three cats in the 5X group, but microscopic examination revealed no histologic abnormalities. No significant changes related to NexGard® COMBO were observed for physical examination, body weight, clinical pathology (hematology, coagulation, and serum chemistry), histopathology, or organ weights.

Study in Heartworm Positive Cats:

Adult cats, 4.7 to 6.6 months of age, were experimentally infected with adult heartworms (D. immitis) by venous transplantation. All cats were negative for heartworm antibody, antigen and microfilariae prior to transplantation. Two weeks after transplantation, immunoserology verified positive antigen and the presence of microfilariae in all enrolled cats. A combination of fipronil, eprinomectin, praziquantel, and (S)-methoprene was applied topically to cats at 1X or 3X the maximum exposure dose once every 28 days for three consecutive treatments; cats in the control group were dosed with mineral oil. One cat in the 1X group exhibited cyanotic mucous membranes and tachypnea for 24 hours following the first treatment. The cat recovered and exhibited no abnormal signs following two subsequent treatments. There was no difference between the treatment groups in the number of adult D. immitis recovered at the end of the study.

Oral Administration Study:

Oral tolerance was evaluated to assess the effects of accidental oral ingestion. Kittens (male and female) ranging in age from 7.4 to 8.9 weeks were orally administered NexGard® COMBO at 1X the maximum exposure dose; kittens in the control group were dosed with saline. Cats were observed for adverse reactions at 1, 2, 3, 4, and 8 hours following administration, then twice a day until Day 14. All 8 cats administered NexGard® COMBO immediately exhibited excessive hypersalivation after oral administration. However, all cats stopped salivating within 1 hour after exposure. No additional health-related observations were seen for the remainder of the study.

How Supplied:

NexGard® COMBO is packaged as a single dose in 0.3 mL (for cats 1.8 – 5.5 lb) and 0.9 mL (for cats 5.6-16.5 lb) applicators.

Each size applicator is available in cartons containing 1, 3 or 6 applications.

Storage Information:

Store at 59° - 86°F (15° - 30°C). Brief periods up to 104°F (40°C) are permitted. Protect from light.

Approved by FDA under NADA # 141-570

Marketed by:

Boehringer Ingelheim Animal Health USA Inc.

Duluth, GA 30096

NEXGARD® is a registered trademark and NEXGARD COMBO is a trademark of Boehringer Ingelheim Animal Health France, used under license.

©2023 Boehringer Ingelheim Animal Health USA Inc. All rights reserved.

184238-003 Rev. 04/2023

Principal Display Panel – 0.3 mL Display Carton

FOR CATS 1.8 – 5.5 LBS 3 Applicators 0.3 mL

NexGard® COMBO

(esafoxolaner, eprinomectin, and praziquantel topical solution)

Apply once a month. Topical solution for cats and kittens 8 weeks of age and older.

Each applicator contains 3.6 mg esafoxolaner, 1.2 mg eprinomectin, and 24.9 mg praziquantel.

CAUTION: Federal law restricts this drug to use by or on the order of a licensed veterinarian.

Approved by FDA under NADA # 141-570

Principal Display Panel – 0.9 mL Display Carton

FOR CATS 5.6 – 16.5 LBS 3 Applicators 0.9 mL

NexGard® COMBO

(esafoxolaner, eprinomectin, and praziquantel topical solution)

Apply once a month. Topical solution for cats and kittens 8 weeks of age and older.

Each applicator contains 10.8 mg esafoxolaner, 3.6 mg eprinomectin, and 74.7 mg praziquantel.

CAUTION: Federal law restricts this drug to use by or on the order of a licensed veterinarian.

Approved by FDA under NADA # 141-570